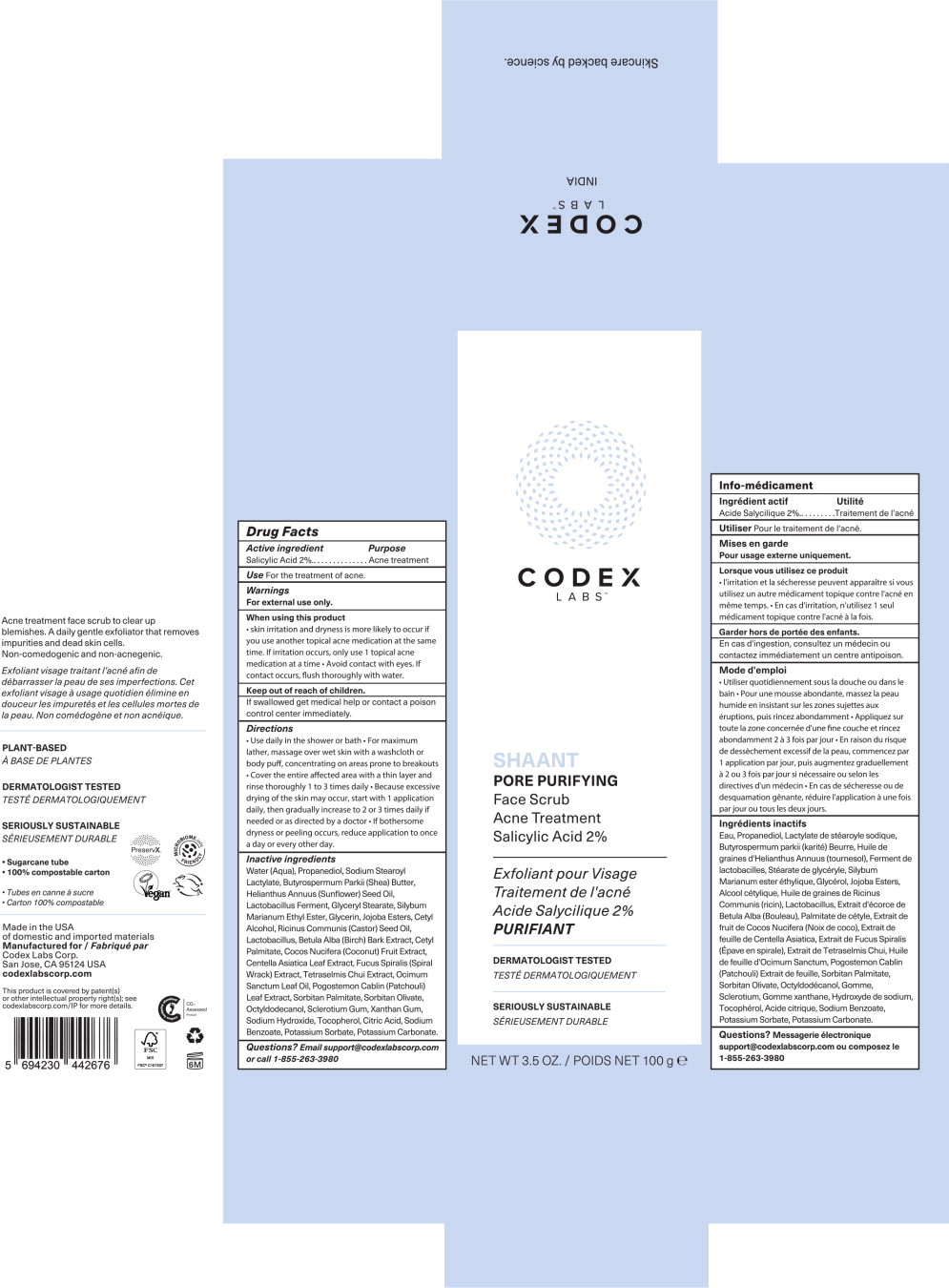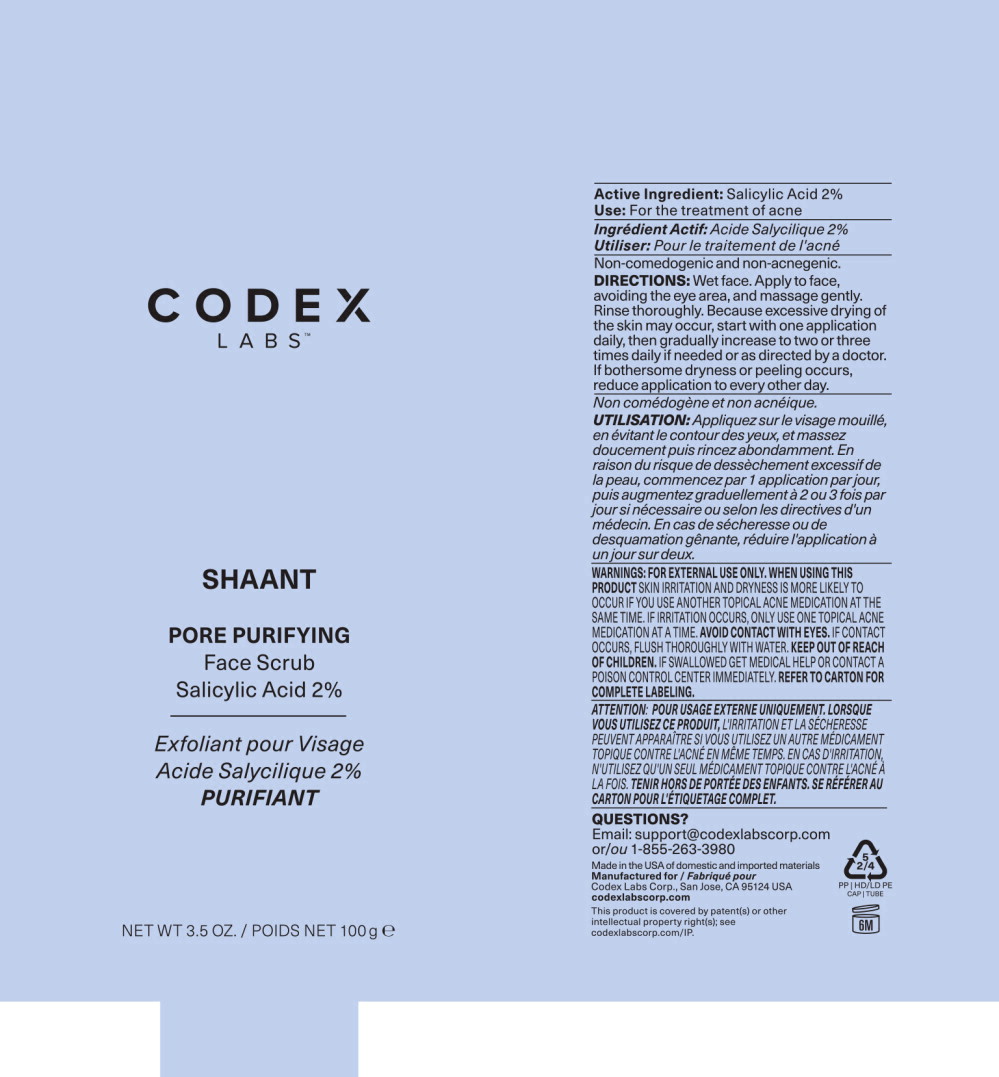 DRUG LABEL: Shaant Pore Purifying Face Scrub
NDC: 83196-676 | Form: CREAM
Manufacturer: Codex Labs Corporation
Category: otc | Type: HUMAN OTC DRUG LABEL
Date: 20251121

ACTIVE INGREDIENTS: SALICYLIC ACID 2 g/100 g
INACTIVE INGREDIENTS: WATER; PROPANEDIOL; SODIUM STEAROYL LACTYLATE; SHEA BUTTER; SUNFLOWER OIL; GLYCERYL MONOSTEARATE; GLYCERIN; HYDROGENATED JOJOBA OIL, RANDOMIZED; CETYL ALCOHOL; CASTOR OIL; BETULA PUBESCENS BARK; CETYL PALMITATE; COCONUT; CENTELLA ASIATICA LEAF; FUCUS SPIRALIS; TETRASELMIS CHUI; OCIMUM TENUIFLORUM LEAF OIL; POGOSTEMON CABLIN TOP; SORBITAN MONOPALMITATE; SORBITAN OLIVATE; OCTYLDODECANOL; BETASIZOFIRAN; XANTHAN GUM; SODIUM HYDROXIDE; TOCOPHEROL; CITRIC ACID MONOHYDRATE; SODIUM BENZOATE; POTASSIUM SORBATE; POTASSIUM CARBONATE; LACTOBACILLUS ACIDOPHILUS; SILYBUM MARIANUM ETHYL ESTER

Drug Facts

Active ingredient

Salicylic Acid 2%

Purpose

Acne treatment

Use

For the treatment of acne.

Warnings

For external use only.

When using this product

- skin irritation and dryness is more likely to occur if you use another topical acne medication at the same time. If irritation occurs, only use 1 topical acne medication at a time
- Avoid contact with eyes. If contact occurs, flush thoroughly with water.

Keep out of reach of children.

If swallowed get medical help or contact a poison control center immediately.

Directions

- Use daily in the shower or bath
- For maximum lather, massage over wet skin with a washcloth or body puff, concentrating on areas prone to breakouts
- Cover the entire affected area with a thin layer and rinse thoroughly 1 to 3 times daily
- Rinse well
- Because excessive drying of the skin may occur, start with 1 application daily, then gradually increase to 2 or 3 times daily if needed or as directed by a doctor
- If bothersome dryness or peeling occurs, reduce application to once a day or every other day.

Inactive ingredients

Water (Aqua), Propanediol, Sodium Stearoyl Lactylate, Butyrospermum Parkii (Shea) Butter, Helianthus Annuus (Sunflower) Seed Oil, Lactobacillus Ferment, Glyceryl Stearate, Silybum Marianum Ethyl Ester, Glycerin, Jojoba Esters, Cetyl Alcohol, Ricinus Communis (Castor) Seed Oil, Lactobacillus, Betula Alba (Birch) Bark Extract, Cetyl Palmitate, Cocos Nucifera (Coconut) Fruit Extract, Centella Asiatica Leaf Extract, Fucus Spiralis (Spiral Wrack) Extract, Tetraselmis Chui Extract, Ocimum Sanctum Leaf Oil, Pogostemon Cablin (Patchouli) Leaf Extract, Sorbitan Palmitate, Sorbitan Olivate, Octyldodecanol, Sclerotium Gum, Xanthan Gum, Sodium Hydroxide, Tocopherol, Citric Acid, Sodium Benzoate, Potassium Sorbate, Potassium Carbonate.

Questions?

Email support@codexlabscorp.com or call 1-855-263-3980

Info-médicament

Ingrédient actif

Acide Salycilique 2%

Utilité

Traitement de l'acné

Utiliser Pour le traitement de l'acné.

Mises en garde

Pour usage externe uniquement.

Lorsque vous utilisez ce produit

- l'irritation et la sécheresse peuvent apparaître si vous utilisez un autre médicament topique contre l'acné en même temps.
- En cas d'irritation, n'utilisez qu'un seul médicament topique contre l'acné à la fois.

Garder hors de portée des enfants.

En cas d'ingestion, consultez un médecin ou contactez immédiatement un centre antipoison.

Mode d'emploi

- Utiliser quotidiennement sous la douche ou dans le bain
- Pour une mousse abondante, massez la peau humide en insistant sur les zones sujettes aux éruptions, puis rincez abondamment
- Appliquez sur toute la zone concernée d'une fine couche et rincez abondamment 2 à 3 fois par jour
- Bien rincer
- En raison du risque de dessèchement excessif de la peau, commencez par 1 application par jour, puis augmentez graduellement à 2 ou 3 fois par jour si nécessaire ou selon les directives d'un médecin
- En cas de sécheresse ou de desquamation gênante, réduire l'application à une fois par jour ou tous les deux jours.

Ingrédients inactifs

Eau, Propanediol, Lactylate de stéaroyle sodique, Butyrospermum parkii (karité) Beurre, Huile de graines d'Helianthus Annuus (tournesol), Ferment de lactobacilles, Stéarate de glycéryle, Silybum Marianum ester éthylique, Glycérol, Jojoba Esters, Alcool cétylique, Huile de graines de Ricinus Communis (ricin), Lactobacillus, Extrait d'écorce de Betula Alba (Bouleau), Palmitate de cétyle, Extrait de fruit de Cocos Nucifera (Noix de coco), Extrait de feuille de Centella Asiatica, Extrait de Fucus Spiralis (Épave en spirale), Extrait de Tetraselmis Chui, Huile de feuille d'Ocimum Sanctum, Pogostemon Cablin (Patchouli) Extrait de feuille, Sorbitan Palmitate, Sorbitan Olivate, Octyldodécanol, Gomme Sclerotium, Gomme xanthane, Hydroxyde de sodium, Tocophérol, Acide citrique, Sodium Benzoate, Potassium Sorbate, Potassium Carbonate.

Questions?

Messagerie électronique support@codexlabscorp.com ou composez le 1-855-2633980

Principal Display Panel – 100g Carton Label

CODEX
LABS™

SHAANT PORE PURIFYING

Face Scrub

Acne Treatment

Salicylic Acid 2%

Exfoliant pour Visage

Traitement de l'acné

Acide Salycilique 2%

PURIFIANT

DERMATOLOGIST TESTED

TESTÉ DERMATOLOGIQUEMENT

SERIOUSLY SUSTAINABLE

SÉRIEUSEMENT DURABLE

NET WT 3.5 OZ. / POIDS NET 100 g e

Principal Display Panel – 100g Tube Label

CODEX
LABS™

SHAANT

PORE PURIFYING

Face Scrub

Salicylic Acid 2%

Exfoliant pour Visage

Acide Salycilique 2%

PURIFIANT

NET WT 3.5 OZ. / POIDS NET 100 g e